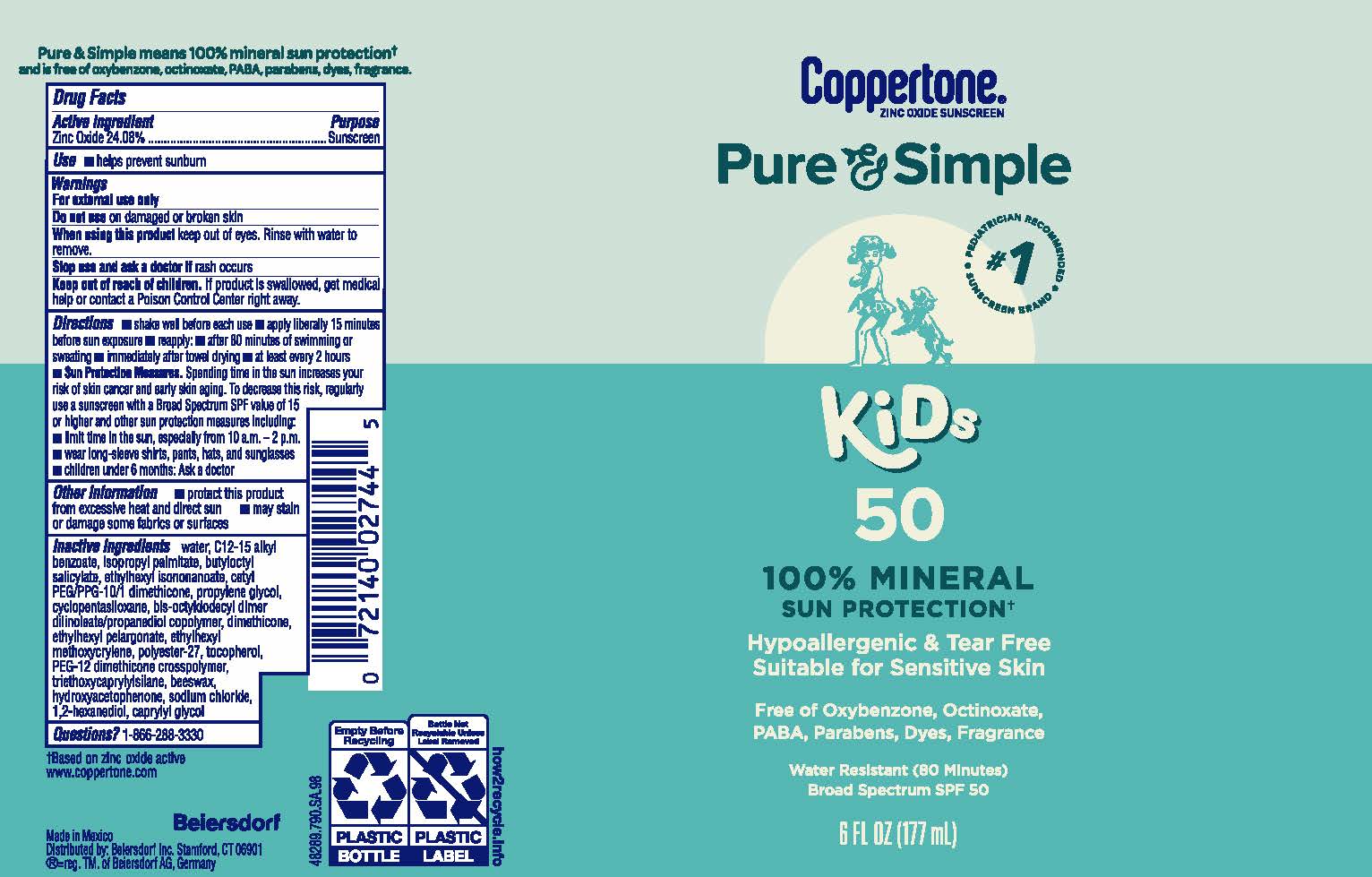 DRUG LABEL: Coppertone Pure and Simple Kids Suncreen SPF 50
NDC: 66800-2744 | Form: LOTION
Manufacturer: Beiersdorf Inc
Category: otc | Type: HUMAN OTC DRUG LABEL
Date: 20251231

ACTIVE INGREDIENTS: AVOBENZONE 24.08 g/100 g
INACTIVE INGREDIENTS: ETHYLHEXYL METHOXYCRYLENE; WATER; 1,2-HEXANEDIOL; ALKYL (C12-15) BENZOATE; SYNTHETIC BEESWAX; CYCLOMETHICONE 5; TRIETHOXYCAPRYLYLSILANE; CAPRYLYL GLYCOL; ETHYLHEXYL PELARGONATE; TOCOPHEROL; POLYESTER-7; DIMETHICONE; SODIUM CHLORIDE; ISOPROPYL PALMITATE; BUTYLOCTYL SALICYLATE; PROPYLENE GLYCOL; BIS-OCTYLDODECYL DIMER DILINOLEATE/PROPANEDIOL COPOLYMER; ETHYLHEXYL ISONONANOATE; CETYL PEG/PPG-10/1 DIMETHICONE (HLB 2); PEG-12 DIMETHICONE (300 CST); HYDROXYACETOPHENONE

Coppertone P&S Kids Lotion SPF 50

Active ingredient

Zinc Oxide 24.08%

Purpose

Sunscreen

Use

■ helps prevent sunburn

Warnings

For external use only

Do not useon damaged or broken skin

WHEN USING

When using this productkeep out of eyes. Rinse with water to remove.

Stop use and ask a doctor ifrash occurs

Keep out of reach of children.If product is swallowed, get medical help or contact a Poison Control Center right away.

Directions

■ shake well before each use

■ apply liberally 15 minutes before sun exposure

■ reapply:

■ after 80 minutes of swimming or sweating

■ immediately after towel drying

■ at least every 2 hours

■ Sun Protection Measures.Spending time in the sun increases your risk of skin cancer and early skin aging. To decrease this risk, regularly use a sunscreen with a Broad Spectrum SPF value of 15 or higher and other sun protection measures including:

■ limit time in the sun, especially from 10 a.m. – 2 p.m.

■ wear long-sleeve shirts, pants, hats, and sunglasses

■ children under 6 months: Ask a doctor

Other information

■ protect this product from excessive heat and direct sun

■ may stain or damage some fabrics or surfaces

Inactive ingredients

water, C12-15 alkyl benzoate, isopropyl palmitate, butyloctyl salicylate, ethylhexyl isononanoate, cetyl PEG/PPG-10/1 dimethicone, propylene glycol, cyclopentasiloxane, bis-octyldodecyl dimer dilinoleate/propanediol copolymer, dimethicone, ethylhexyl pelargonate, ethylhexyl methoxycrylene, polyester-27, tocopherol, PEG-12 dimethicone crosspolymer, triethoxycaprylylsilane, beeswax, hydroxyacetophenone, sodium chloride, 1,2-hexanediol, caprylyl glycol

Questions?

1-866-288-3330

PACKAGE LABEL

Coppertone®

Zinc Oxide Sunscreen

Pure&Simple

#1 Pediatrician Recommended Sunscreem Brand

100% Mineral Sun Protection

Hypoallergenic & Tear Free

Suitable for Sensitive Skin

Free of Oxybenzone, Octinoxate, PABA, Parabens, Dyes, Fragrance

Water Resistant (80 Minutes)

Broad Spectrum SPF 50